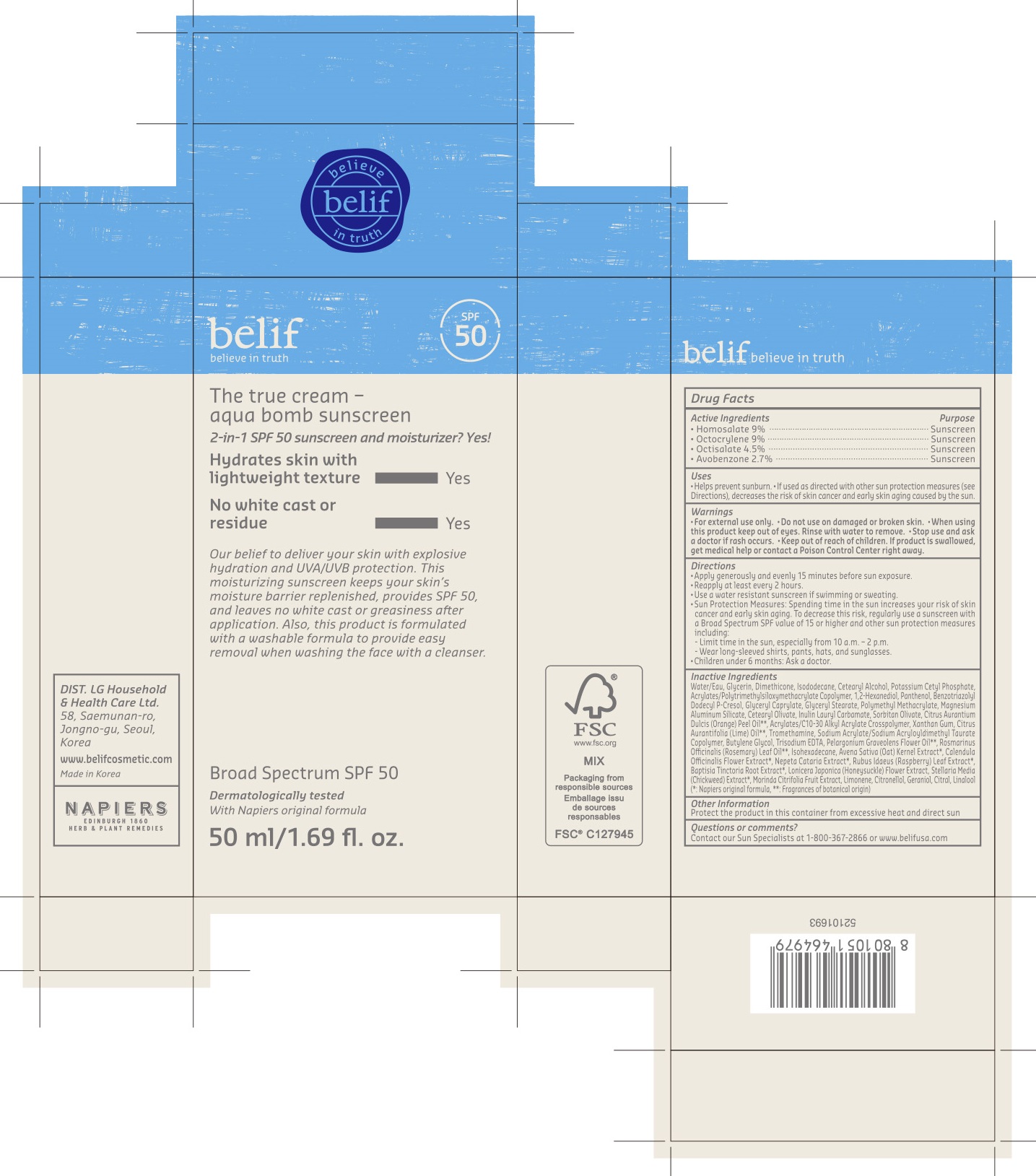 DRUG LABEL: belif The true cream aqua bomb sunscreen Broad Spectrum SPF 50
NDC: 72330-710 | Form: CREAM
Manufacturer: fmg Co.Ltd
Category: otc | Type: HUMAN OTC DRUG LABEL
Date: 20250101

ACTIVE INGREDIENTS: OCTISALATE 4.5 g/50 mL; HOMOSALATE 9 g/50 mL; AVOBENZONE 2.7 g/50 mL; OCTOCRYLENE 9 g/50 mL
INACTIVE INGREDIENTS: WATER

72330-710-01 belif The true cream aqua bomb sunscreen Broad Spectrum SPF 50

ACTIVE INGREDIENTS

Avobenzone 2.7%
Homosalate 9%
Octisalate 4.5%
Octocrylene 9%

PURPOSE

SUNSCREEN

USES

- Helps prevent sunburn
- If used as directed with other sun protection measures (see Directions), decreases the risk of skin cancer and early skin aging caused by the sun

WARNINGS

For external use only

- Do not useon damaged or broken skin.

WHEN USING

- When using this productkeep out of eyes. Rinse with water to remove.

- Stop use and ask doctorif rash occurs.

- Keep out of reach of children.If product is swallowed, get medical help or contact a Poison Control Center right away.

DIRECTIONS

- Apply generously and evenly 15 minutes before sun exposure and as needed.
- Reapply as needed or after towel drying, swimming, or sweating.
- Sun Protection Measures.Spending time in the sun increases your risk of skin cancer and early skin aging. To decrease this risk, regularly use a sunscreen with a Broad Spectrum SPF value of 15 or higher and other sun protection measures including:

- Limit time in the sun, especially from 10 a.m. to 2 p.m.

- Wear long-sleeved shirts, pants, hats, and sunglasses.

- Children under 6 months: Ask a doctor.

INACTIVE INGREDIENTS

WATER, GLYCERIN,

OTHER INFORMATION

Protect the product in this container from excessive heat and direct sun

QUESTIONS OR COMMENTS?

Contact our Sun Specialist at 1-888-367-2866or www.belifusa.com

PRINCIPAL DISPLAY PANEL

belif
believe in truth
The true cream -
aqua bomb sunscreen
2-in-1 SPF 50 sunscreen and moisturizer? Yes!
Hydrates skin with
lightweight texture ------------- Yes
No white cast or
residue ------------- Yes
Our belief to deliver your skin with explosive
hydration and UVA/UVB protection. This
moisturizing sunscreeen keeps your skin's
moisture barrier replenished, provides SPF 50,
and leaves no white cast or greasiness after
application. Also, this product is formulated
with a washable formula to provide easy
removal when washing the face with a cleanser.
Broad Spectru SPF 50
Dermatologically tested
With Napiers original formula
50 ml/1.69 fl. oz.